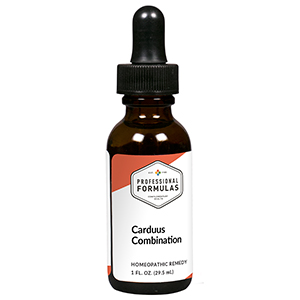 DRUG LABEL: Carduus Combination
NDC: 63083-9215 | Form: LIQUID
Manufacturer: Professional Complementary Health Formulas
Category: homeopathic | Type: HUMAN OTC DRUG LABEL
Date: 20190815

ACTIVE INGREDIENTS: AMARYLLIS BELLADONNA WHOLE 10 [hp_X]/29.5 mL; CHOLESTEROL 10 [hp_X]/29.5 mL; SULFUR 10 [hp_X]/29.5 mL; OYSTER SHELL CALCIUM CARBONATE, CRUDE 10 [hp_X]/29.5 mL; MILK THISTLE 10 [hp_X]/29.5 mL; CHELIDONIUM MAJUS WHOLE 10 [hp_X]/29.5 mL; CINCHONA OFFICINALIS BARK 10 [hp_X]/29.5 mL; LYCOPODIUM CLAVATUM SPORE 10 [hp_X]/29.5 mL; TARAXACUM OFFICINALE 10 [hp_X]/29.5 mL; VERATRUM ALBUM ROOT 10 [hp_X]/29.5 mL
INACTIVE INGREDIENTS: ALCOHOL; WATER

R215

ACTIVE INGREDIENTS

Belladonna 10X, 30X, 200X, 1000X
Cholesterinum 10X, 30X
Sulphur 10X, 30X
and all the following at 10X, 30X, 200X:
Calcarea carbonica
Carduus marianus
Chelidonium majus
Cinchona officinalis
Lycopodium clavatum
Taraxacum officinale
Veratrum album

QUESTIONS

Professional Formulas

PO Box 2034 Lake Oswego, OR 97035

INDICATIONS

For the temporary relief of flatulence, indigestion, abdominal pain or cramping, or nausea.*

PURPOSE

*Claims based on traditional homeopathic practice, not accepted medical evidence. Not FDA evaluated.

WARNINGS

If symptoms do not improve or are accompanied by a fever, consult a doctor. Keep out of the reach of children. In case of overdose, get medical help or contact a poison control center right away. If pregnant or breastfeeding, ask a healthcare professional before use.

Keep out of the reach of children.

PREGNANCY OR BREAST FEEDING

If pregnant or breastfeeding, ask a healthcare professional before use.

DIRECTIONS

Place drops under tongue 30 minutes before/after meals. Adults and children 12 years and over: Take 10 drops up to 3 times per day. Consult a physician for use in children under 12 years of age.

OTHER INFORMATION

Tamper resistant. If seal is broken, do not use. After opening, close container tightly and store at room temperature away from heat.

INACTIVE INGREDIENTS

40% ethanol, purified water.

LABEL

Est 1985

Professional Formulas

Complementary Health

Carduus Combination

Homeopathic Remedy

1 FL. OZ. (29.5 mL)